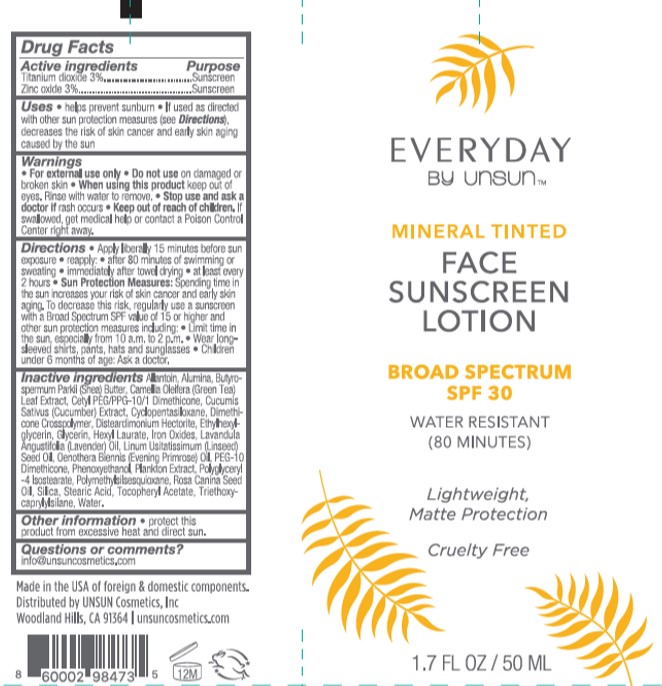 DRUG LABEL: Unsun
NDC: 58443-0389 | Form: LOTION
Manufacturer: Prime Enterprises, Inc.
Category: otc | Type: HUMAN OTC DRUG LABEL
Date: 20210115

ACTIVE INGREDIENTS: TITANIUM DIOXIDE 31.5 mg/1 mL; ZINC OXIDE 31.5 mg/1 mL
INACTIVE INGREDIENTS: POLYMETHYLSILSESQUIOXANE (4.5 MICRONS); SILICON DIOXIDE; LINSEED OIL; PHENOXYETHANOL; FERRIC OXIDE RED; LAVENDER OIL; PEG-10 DIMETHICONE (600 CST); ALUMINUM OXIDE; SHEA BUTTER; CAMELLIA OLEIFERA LEAF; PHYSALIS ANGULATA; POLYGLYCERYL-4 ISOSTEARATE; ROSA CANINA SEED; STEARIC ACID; EVENING PRIMROSE OIL; ALLANTOIN; DISTEARDIMONIUM HECTORITE; GLYCERIN; CETYL PEG/PPG-10/1 DIMETHICONE (HLB 2); CUCUMBER SEED; CYCLOMETHICONE 5; ALPHA-TOCOPHEROL ACETATE; TRIETHOXYCAPRYLYLSILANE; WATER; ETHYLHEXYLGLYCERIN; HEXYL LAURATE

Unsun Mineral Tinted Face Sunscreen Lotion Broad Spectrum SPF 30

Active ingredients

Titanium Dioxide 3%

Zinc Oxide 3%

Purpose

Sunscreen

Uses

helps prevent sunburn

If used as directed with other sun protection measures (see Directions), decreases the risk of skin cancer and early skin aging caused by the sun

Warnings

For external use only

Do not use

on damaged or broken skin

When using this product

keep out of eyes. Rinse with water to remove.

Stop use and ask a doctor

if rash occurs

Keep out of reach of children.

If swallowed, get medical help or contact a Poison Control Center right away.

Directions

Apply liberally 15 minutes before sun exposure

reapply:

after 80 minutes of swimming or sweating

immediately after towel drying

at least every 2 hours

Sun Protection Measures: Spending time in the sun increases your risk of skin cancer and early skin aging. To decrease this risk, regularly use a suncreen with a Broad Spectrum SPF value of 15 or higher and other sun protection measures including:

Limit time in the sun, especially from 10 a.m. to 2 p.m.

Wear long-sleeved shirts, pants, hats and sunglasses

Children under 6 months of age: Ask a doctor.

Inactive ingredients

Allantoin, Alumina, Butyrospermum Parkii (Shea) Butter, Camellia Oleifera (Green Tea) Leaf Extract, Cetyl PEG/PPG-10/1 Dimethicone, Cucumis Sativus (Cucumber) Extract, Cyclopentasiloxane, Dimethicone Crosspolymer, Disteardimonium Hectorite, Ethylhexylglycerin, Glycerin, Hexyl Laurate, Iron Oxides, Lavandula Angustifolia (Lavender) Oil, Linum Usitatissimum (Linseed) Seed Oil, Oenothera Biennis (Evening Primrose) Oil, PEG-10 Dimethicone, Phenoxyethanol, Plankton Extract, Polyglyceryl-4 Isostearate, Polymethylsilsesquioxane, Rosa Canina Seed Oil, Silica, Stearic Acid, Tocopheryl Acetate, Triethoxycaprylylsilane, Water

Other information

protect this product from excessive heat and direct sun.

Questions or comments?

info@unsuncosmetics.com